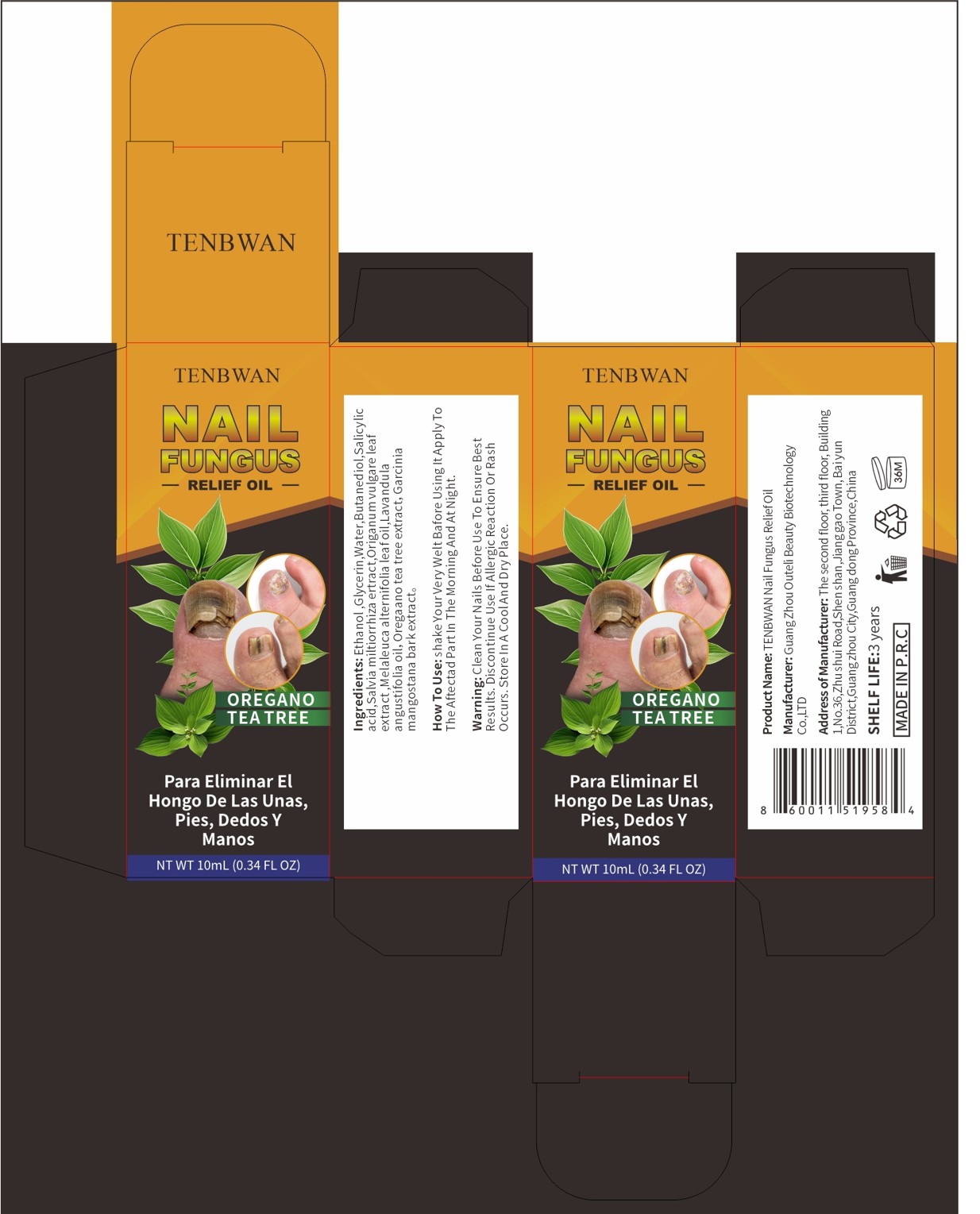 DRUG LABEL: TENBWAN NAIL FUNGUS RELIEF Oil
NDC: 84458-002 | Form: LIQUID
Manufacturer: Dongguan LeTaoHui CrossBorder Ecommerce Co.
Category: otc | Type: HUMAN OTC DRUG LABEL
Date: 20240824

ACTIVE INGREDIENTS: SALVIA MILTIORRHIZA WHOLE 0.7 g/100 mL; GREEN TEA LEAF 2.4 g/100 mL; LAVANDULA ANGUSTIFOLIA (LAVENDER) OIL 0.2 g/100 mL; MELALEUCA ALTERNIFOLIA (TEA TREE) LEAF OIL 0.2 g/100 mL; OREGANO 0.7 g/100 mL; GARCINIA MANGOSTANA BARK 0.6 g/100 mL
INACTIVE INGREDIENTS: SALICYLIC ACID; WATER; BUTANEDIOL (MIXED ISOMERS); GLYCERIN; ALCOHOL

TENBWAN NAIL FUNGUS RELIEF OIL

ACTIVE INGREDIENT

Salvia miltiorrhiza ertract
Origanum vulgare leaf extract
Melaleuca alternifolia leaf oil
Lavandula angustifolia oil
Oregaano tea tree extract
garcinia mangostana bark extract

PURPOSE

Para Eliminar ElHongo De Las Unas,Pies, Dedos YManos

KEEP OUT OF REACH OF CHILDREN SECTION

INDICATIONS AND USAGE

Para Eliminar ElHongo De Las Unas,Pies, Dedos YManos

WARNINGS

Warning: Clean Your Nails Before Use To Ensure BestResults. Discontinue Use lf Allergic Reaction Or RashOccurs.StoreInA CoolAnd DryPlace.

DOSAGE AND ADMINISTRATION

How To Use: shake Your Very Welt Bafore Using lt Apply To The Aftectad Partin The Morning And At Night.

INACTIVE INGREDIENT

Ethanol
Glycerin
Water
Butanediol
Salicylic acid